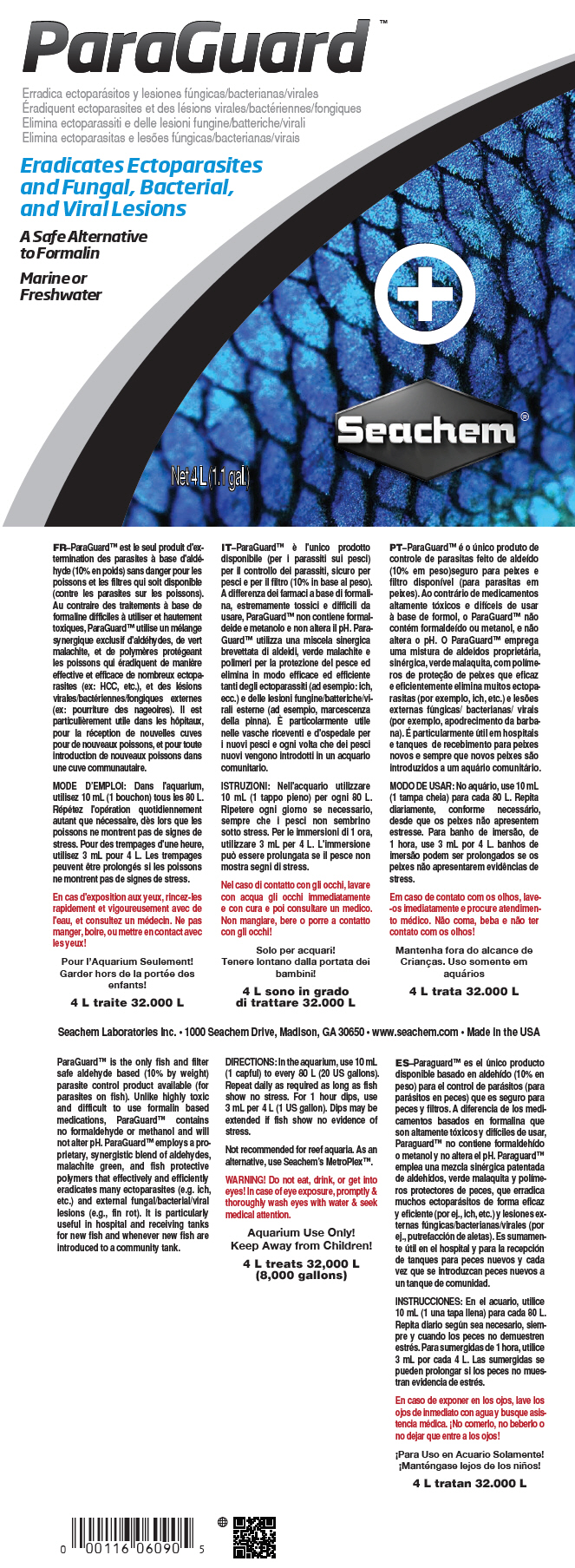 DRUG LABEL: Paraguard
NDC: 55999-061 | Form: LIQUID
Manufacturer: Seachem Laboratories Inc.
Category: animal | Type: OTC ANIMAL DRUG LABEL
Date: 20190807

ACTIVE INGREDIENTS: GLUTARAL 25 mg/1 mL; Malachite Green 0.04 mg/1 mL

Paraguard™

VETERINARY INDICATIONS

ParaGuard™ is the only fish and filter safe aldehyde based (10% by weight) parasite control product available (for parasites on fish). Unlike highly toxic and difficult to use formalin based medications, ParaGuard™ contains no formaldehyde or methanol and will not alter pH. ParaGuard™ employs a proprietary, synergistic blend of aldehydes, malachite green, and fish protective polymers that effectively and efficiently eradicates many ectoparasites (e.g. ich, etc.) and external fungal/bacterial/viral lesions (e.g., fin rot). It is particularly useful in hospital and receiving tanks for new fish and whenever new fish are introduced to a community tank.

DOSAGE AND ADMINISTRATION

DIRECTIONS: In the aquarium, use 10 mL (1 capful) to every 80 L (20 US gallons). Repeat daily as required as long as fish show no stress. For 1 hour dips, use 3 mL per 4 L (1 US gallon). Dips may be extended if fish show no evidence of stress.

Not recommended for reef aquaria. As an alternative, use Seachem's MetroPlex™.

WARNINGS

WARNING! Do not eat, drink, or get into eyes! In case of eye exposure, promptly & thoroughly wash eyes with water & seek medical attention.

SAFE HANDLING WARNING

Aquarium Use Only!

Keep Away from Children!

4 L treats 32,000 L
(8,000 gallons)

Seachem Laboratories Inc. • 1000 Seachem Drive, Madison, GA 30650 • www.seachem.com • Made in the USA

PRINCIPAL DISPLAY PANEL - 4 L Bottle Label

ParaGuard™

Eradicates Ectoparasites
and Fungal, Bacterial,
and Viral Lesions

A Safe Alternative
to Formalin

Marine or
Freshwater

Net 4 L (1.1 gal.)

Seachem®